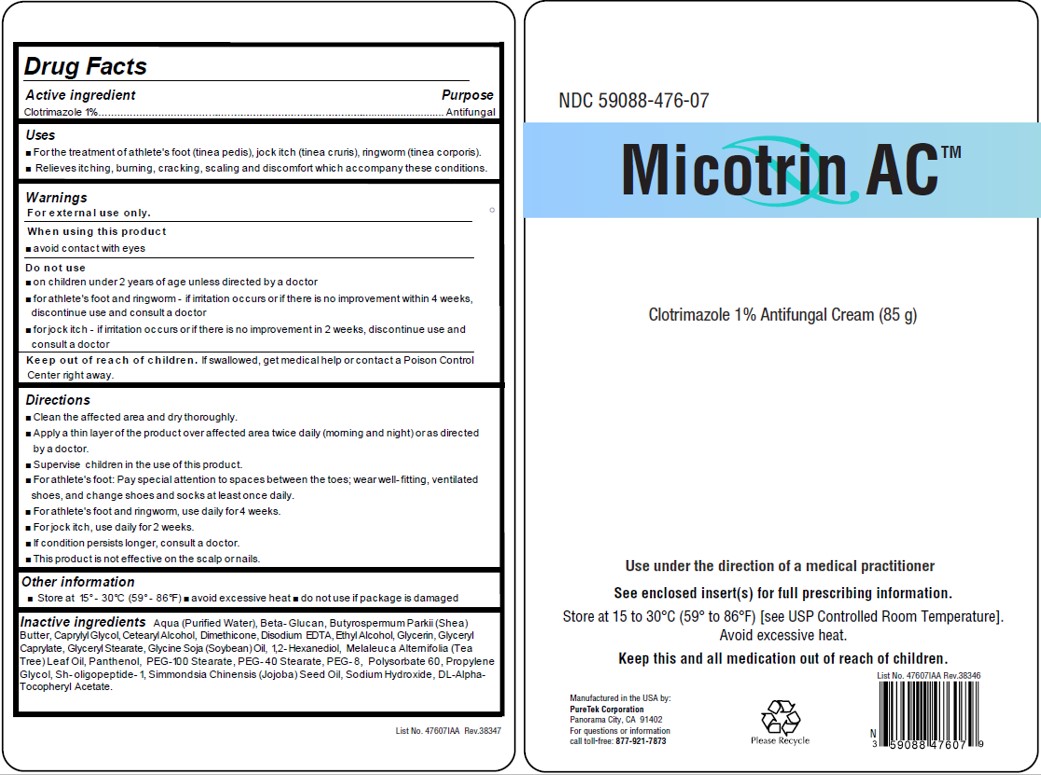 DRUG LABEL: Micotrin AC
NDC: 59088-476 | Form: CREAM
Manufacturer: PureTek Corporation
Category: otc | Type: HUMAN OTC DRUG LABEL
Date: 20241001

ACTIVE INGREDIENTS: CLOTRIMAZOLE 10 mg/1 g
INACTIVE INGREDIENTS: WATER; DIMETHICONE; TEA TREE OIL; NEPIDERMIN; SODIUM HYDROXIDE; POLYETHYLENE GLYCOL 400; SOYBEAN OIL; PANTHENOL; CURDLAN; SHEA BUTTER; CAPRYLYL GLYCOL; EDETATE DISODIUM ANHYDROUS; .ALPHA.-TOCOPHEROL ACETATE, DL-; ALCOHOL; GLYCERIN; GLYCERYL CAPRYLATE; GLYCERYL MONOSTEARATE; 1,2-HEXANEDIOL; PEG-100 STEARATE; PROPYLENE GLYCOL; JOJOBA OIL; PEG-40 STEARATE; CETOSTEARYL ALCOHOL; POLYSORBATE 60

Micotrin AC™
(Clotrimazole 1% Antifungal Cream)
10/19- Updatng marketing date to 10/25 v2

Drug Facts

Active ingredient

Clotrimazole 1%

Purpose

Antifungal

Uses

- For the treatment of athlete's foot (tinea pedis), jock itch (tinea cruris), ringworm (tinea corporis).
- Relieves itching, burning, cracking, scaling, and discomfort which accompanies these conditions.

Warnings

For external use only.

When using this product avoid contact with eyes

Do not use

- on children under 2 years of age unless directed by a doctor
- for athlete's foot and ringworm - if irritation occurs or if there is no improvement within 4 weeks, discontinue use and consult a doctor
- for jock itch - if irritation occurs or if there is no improvement in 2 weeks, discontinue use and consult a doctor

Keep out of reach of children. If swallowed, get medical help or contact a Poison Control Center right away.

Directions

- Clean the affected area and dry thoroughly.
- Apply a thin layer of the product over the affected area twice daily (morning and night) or as directed by a doctor.
- Supervise children in the use of this product.
- For athlete's foot: Pay special attention to spaces between the toes; wear well-fitting, ventilated shoes, and change shoes and socks at least once daily.
- For athlete's foot and ringworm, use daily for 4 weeks.
- For jock itch, use daily for 2 weeks.
- If condition persists longer, consult a doctor.
- his product is not effective on the scalp or nails.

Use under the direction of a medical practitioner

Other information

■ Store at 15° - 30°C (59° - 86°F) ■ avoid excessive heat ■ do not use if package is damaged

Inactive ingredients

Aqua (Purified Water), Beta-Glucan, Butyrospermum Parkii (Shea) Butter, Caprylyl Glycol, Cetearyl Alcohol, Dimethicone, Disodium EDTA, Ethyl Alcohol, Glycerin, Glyceryl Caprylate, Glyceryl Stearate, Glycine Soja (Soybean) Oil, 1,2-Hexanediol, Melaleuca Alternifolia (Tea Tree) Leaf Oil, Panthenol, PEG-100 Stearate, PEG-40 Stearate PEG-8, Polysorbate 60, Propylene Glycol, Sholigopeptide-1, Simmondsia Chinensis (Jojoba) Seed Oil, Sodium Hydroxide, DL-Alpha-Tocopheryl Acetate

Micotrin ACTM

Manufactured in the USA by:
PureTek Corporation
Panorama City, CA 91402
For questions or information
call toll-free: 877-921-7873